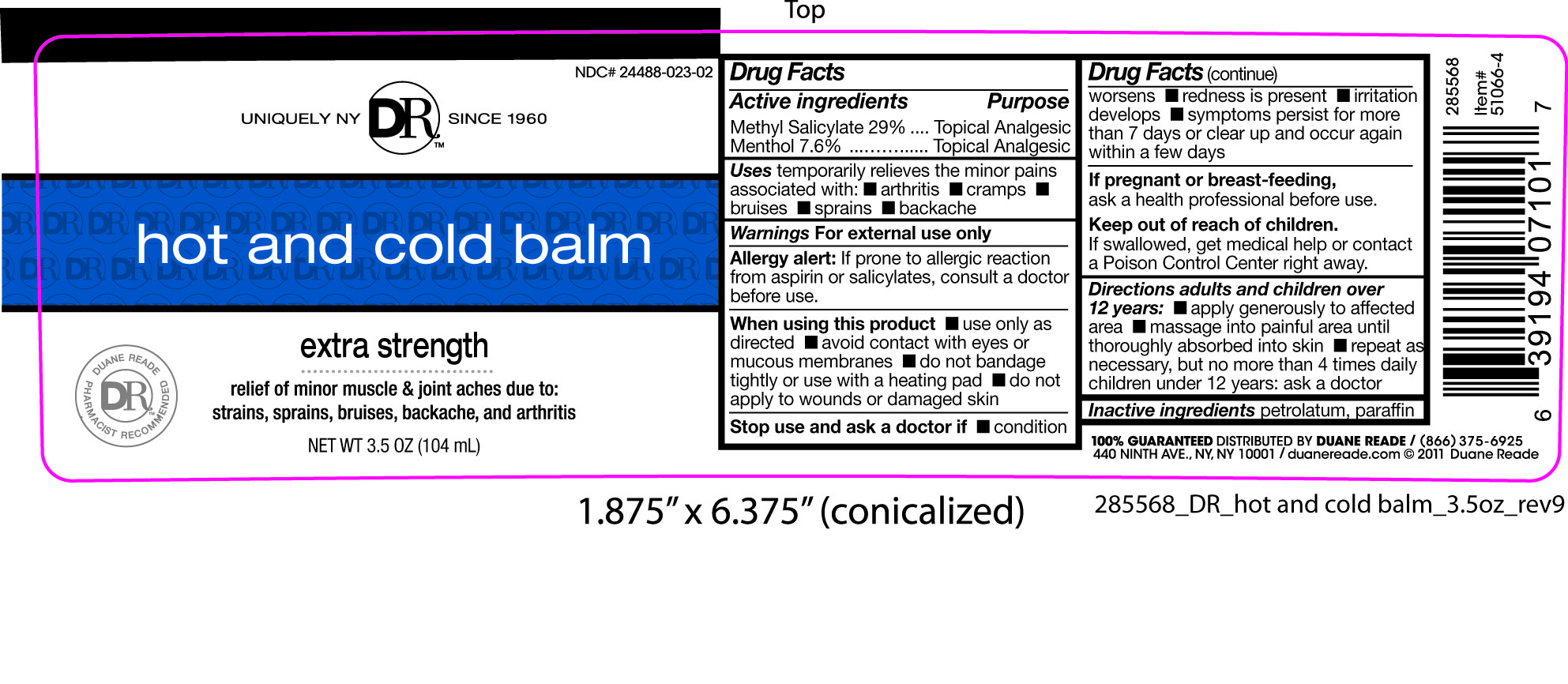 DRUG LABEL: Duane Reade
NDC: 24488-023 | Form: SALVE
Manufacturer: Duane Reade
Category: otc | Type: HUMAN OTC DRUG LABEL
Date: 20110228

ACTIVE INGREDIENTS: METHYL SALICYLATE 30.16 mL/104 mL; MENTHOL 7.90 mL/104 mL
INACTIVE INGREDIENTS: PETROLATUM; PARAFFIN

Drug Facts

Active Ingredients Purpose

Methyl Salicylate 29% ...Topical Analgesic
Menthol 7.6% ................Topical Analgesic

Uses

temporarily relieves the minor pains associated with:

- arthritis
- cramps
- bruises
- sprains
- backache

Warnings

For external use only

Allergy alert:

If prone to allergic reaction from aspirin or salicylates, consult a doctor before use.

When using this product

- use only as directed
- avoid contact with eyes or mucous membranes
- do not bandage tightly or with a heating pad
- do not apply to wounds or damaged skin

Stop use and ask a doctor if

- condition worsens
- redness is present
- irritation develops
- symptoms persist for more than 7 days or clear up and occur again within a few days

If pregnant or breast-feeding,

ask a health professional before use.

Keep out of reach of children.

If swallowed, get medical help or contact a Poison Control Center right away.

Directions adults and children over 12 years:

- apply generously to affected area
- massage into painful area until thoroughly absorbed into skin
- repeat as necessary, but no more than 4 times daily

children under 12 years: ask a doctor.

Inactive ingredients

petrolatum, paraffin

PACKAGE LABEL

Placeholder text